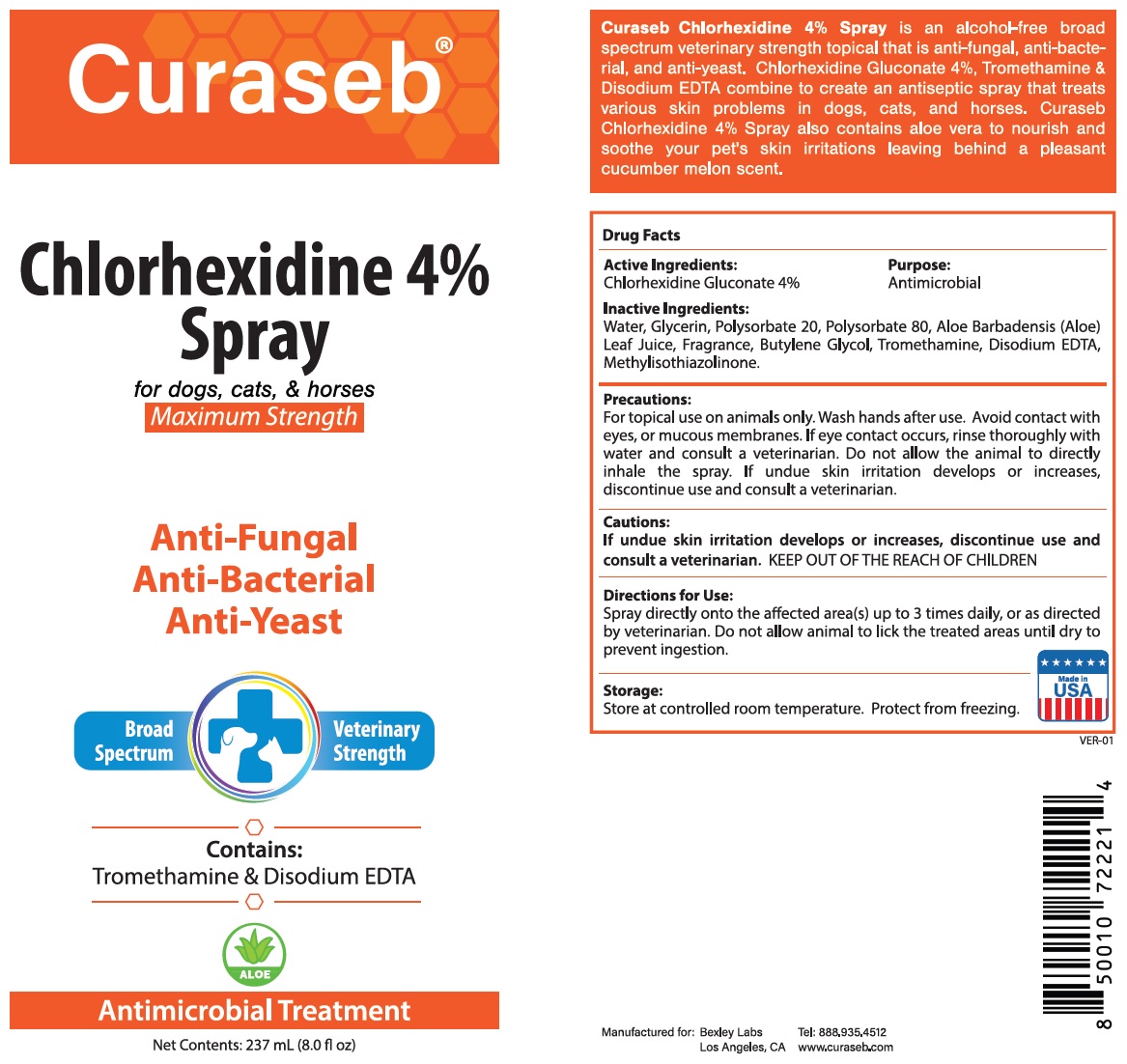 DRUG LABEL: Curaseb Chlorhexidine 4%
NDC: 86133-104 | Form: SPRAY
Manufacturer: Bexley Labs
Category: animal | Type: OTC ANIMAL DRUG LABEL
Date: 20230223

ACTIVE INGREDIENTS: CHLORHEXIDINE GLUCONATE 4 g/100 mL
INACTIVE INGREDIENTS: WATER; GLYCERIN; POLYSORBATE 20; POLYSORBATE 80; ALOE VERA LEAF; BUTYLENE GLYCOL; TROMETHAMINE; EDETATE DISODIUM ANHYDROUS; METHYLISOTHIAZOLINONE

Curaseb® Chlorhexidine 4% Spray

Active Ingredients:

Chlorhexidine Gluconate 4%

Purpose:

Antimicrobial

INDICATIONS AND USAGE

Curaseb Chlorhexidine 4% Spray is an alcohol-free broad spectrum veterinary strength topical that is anti-fungal, anti-bacterial, and anti-yeast. Chlorhexidine Gluconate 4%, Tromethamine & Disodium EDTA combine to create an antiseptic spray that treats various skin problems in dogs, cats, and horses. Curaseb Chlorhexidine 4% Spray also contains aloe vera to nourish and soothe your pet's skin irritations leaving behind a pleasant cucumber melon scent.

Inactive Ingredients:

Water, Glycerin, Polysorbate 20, Polysorbate 80, Aloe Barbadensis (Aloe) Leaf Juice, Fragrance, Butylene Glycol, Tromethamine, Disodium EDTA, Methylisothiazolinone.

Precautions:

For topical use on animals only. Wash hands after use. Avoid contact with eyes, or mucous membranes. If eye contact occurs, rinse thoroughly with water and consult a veterinarian. Do not allow the animal to directly inhale the spray.

Cautions:

If undue skin irritation develops or increases, discontinue use and consult a veterinarian.

KEEP OUT OF THE REACH OF CHILDREN

Directions for Use:

Spray directly onto the affected area(s) up to 3 times daily, or as directed by veterinarian. Do not allow animal to lick the treated areas until dry to prevent ingestion.

Storage:

Store at controlled room temperature. Protect from freezing.

for dogs, cats & horses

Maximum Strength

ALOE

Antimicrobial Treatment

Made in USA

Manufactured for: Bexley Labs
Los Angeles, CA

Tel: 888.935.4512
www.curaseb.com